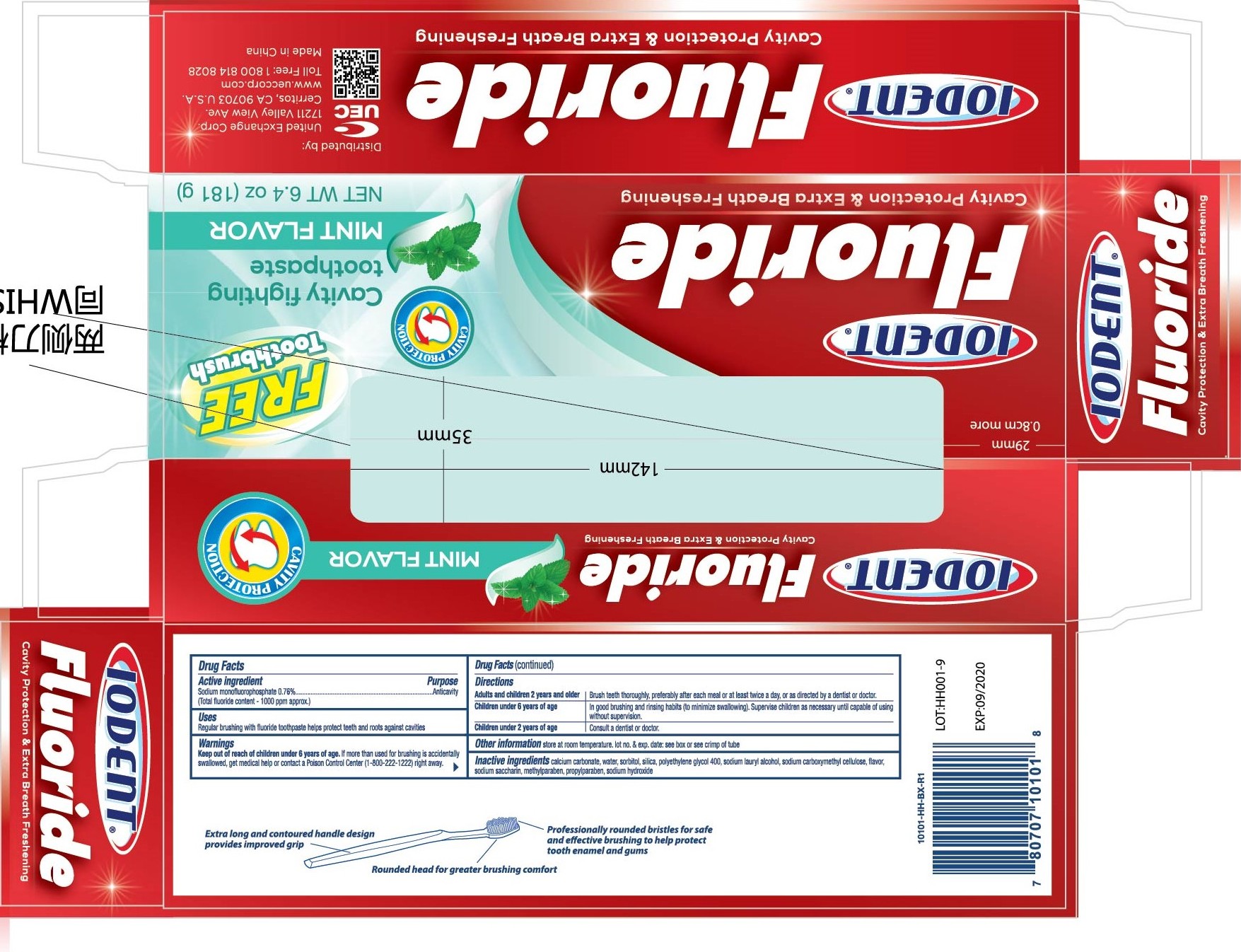 DRUG LABEL: IODENT tooth
NDC: 72129-001 | Form: PASTE
Manufacturer: Zhaoqing Longda Biotechnology Co., Ltd.
Category: otc | Type: HUMAN OTC DRUG LABEL
Date: 20220215

ACTIVE INGREDIENTS: SODIUM MONOFLUOROPHOSPHATE 0.76 g/100 g
INACTIVE INGREDIENTS: SODIUM HYDROXIDE; CALCIUM CARBONATE; SODIUM SILICATE; SORBITOL; POLYETHYLENE GLYCOL 400; PROPYPERONE; SODIUM CARBOXYMETHYL .BETA.-GLUCAN (DS 0.65-0.85); POTASSIUM SODIUM SACCHARATE; WATER; METHYLPARABEN; SODIUM LAURYL SULFATE

72129 001

Active Ingredient

sodium monofluorphosphate 0.76%

Purpose

Anticavity

Use

Regular brushing with fluoride toothpaste helps protect teeth and roots against cavities

Warning

Keep out of reach under 6 years of age. If more than used for brushing is accidentally swallowed, get medical help or contact a Poison Control Center (1-800-222-1222) right away.

Directions

Adults and children 2 years and older brush teeth thoroughly, preferably after each meal or as least twice a day , or as directly by a dentist or doctor

Children under 6 years of age In good brushing and rinsing habits (to minimize swallowing). Supervise children as necessary until capable of using without supervision

Children under 2 years of age Consult a dentist or doctor

Inactive Ingredients

calcium carbonate , water, sorbitol , silica, polyethylene glycol 400, sodium laury alcohol, sodium carboxymethyl cellulose, flavor, sodium saccharin, methylparaben, propyparaben , sodium hydroxide

Keep out of reach of children under 6 years of age